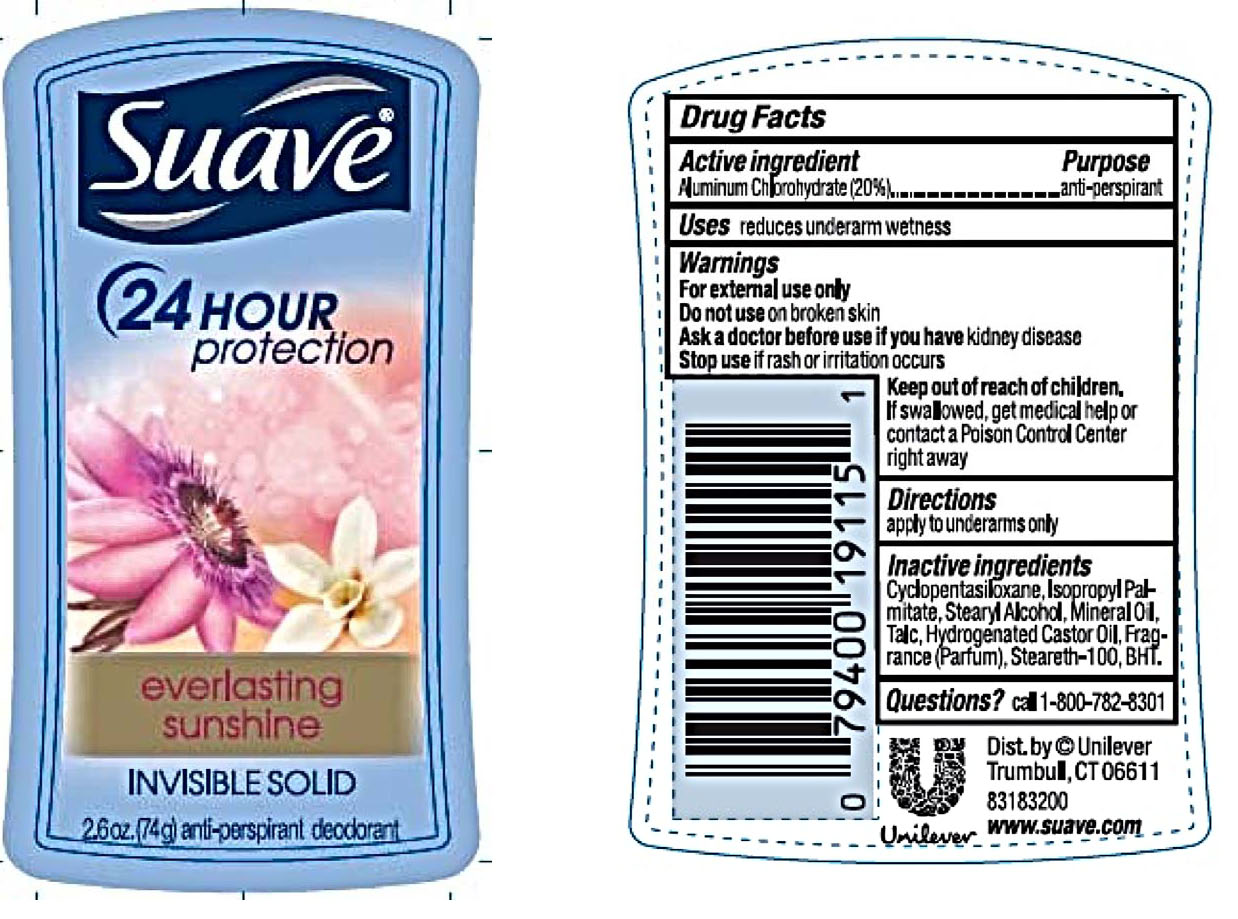 DRUG LABEL: Suave
NDC: 64942-1631 | Form: STICK
Manufacturer: Conopco Inc. d/b/a/ Unilever
Category: otc | Type: HUMAN OTC DRUG LABEL
Date: 20221207

ACTIVE INGREDIENTS: ALUMINUM CHLOROHYDRATE 20 g/100 g
INACTIVE INGREDIENTS: PEG-8 DISTEARATE; TALC; CYCLOMETHICONE 5; ISOPROPYL PALMITATE; BUTYLATED HYDROXYTOLUENE; MINERAL OIL; STEARYL ALCOHOL; STEARETH-100

Suave 24 Hour Protection Everlasting Sunshine Invisible Solid Anti-Perspirant Deodorant

SUAVE 24 HOUR PROTECTION EVERLASTING SUNSHINE INVISIBLE SOLID ANTI-PERSPIRANT DEODORANT - aluminum chlorohydrate liquid

Suave 24 Hour Protection Everlasting Sunshine Invisible Solid Anti-Perspirant Deodorant

Drug Facts

Active ingredient

Aluminum Chlorohydrate (20.0%)

Purpose

antiperspirant

Uses

• reduces underarm wetness

Warnings

• For external use only.
• Do not use on broken skin .
• Ask a doctor before use if you have kidney disease.
• Stop use if rash or irritation occurs.

• Keep out of reach of children.

If swallowed, get medical help or contact a Poison Control Center right away.

Directions

apply to underarms only

Inactive ingredients

Cyclopentasiloxane, Stearyl Alcohol, PPG-14 Butyl Ether, Hydrogenated Castor Oil, Talc, PEG-8 Distearate, Fragrance (Parfum), BHT.

Questions?

Call toll-free 1-800-782-8301